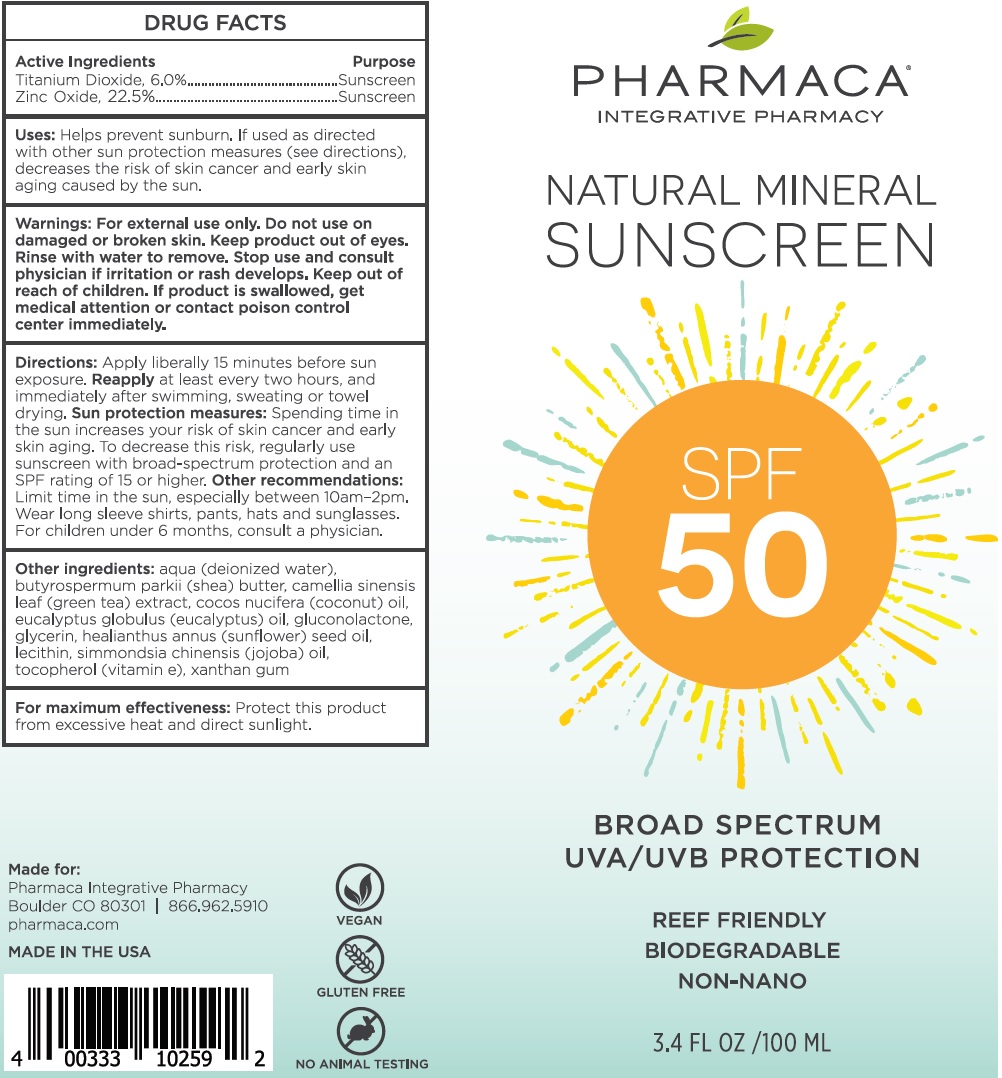 DRUG LABEL: PHARMACA Natural Mineral Sunscreen SPF-50
NDC: 62082-057 | Form: CREAM
Manufacturer: Pharmaca Integrative Pharmacy, Inc.
Category: otc | Type: HUMAN OTC DRUG LABEL
Date: 20231105

ACTIVE INGREDIENTS: TITANIUM DIOXIDE 60 mg/1 mL; ZINC OXIDE 225 mg/1 mL
INACTIVE INGREDIENTS: WATER; SHEA BUTTER; GREEN TEA LEAF; COCONUT OIL; EUCALYPTUS OIL; GLUCONOLACTONE; GLYCERIN; HELIANTHUS ANNUUS FLOWERING TOP; JOJOBA OIL; .ALPHA.-TOCOPHEROL; XANTHAN GUM

PHARMACA Natural Mineral Sunscreen SPF-50

Active Ingredients

Titanium Dioxide, 6.0%

Zinc Oxide, 22.5%

Purpose

Sunscreen

Uses:

Helps prevent sunburn. If used as directed with other sun protection measures (see directions), decreases the risk of skin cancer and early skin aging caused by the sun.

Warnings:

For external use only.

Do not use

on damaged or broken skin. Keep product out of eyes. Rinse with water to remove.

Stop use and consult physician

if irritation or rash develops.

Keep out of reach of children.

If product is swallowed, get medical attention or contact poison control center immediately.

Directions:

Apply liberally 15 minutes before sun exposure. at least every two hours, and immediately after swimming, sweating or towel drying. Spending time in the sun increases your risk of skin cancer and early skin aging. To decrease this risk, regularly use sunscreen with broad-spectrum protection and an SPF rating of 15 or higher. Limit time in sleeve shirts, pants, hats and sunglasses. For children under 6 months, consult a physician. Reapply Sun protection measures: Other recommendations:

Other ingredients:

aqua (deionized water), butyrospermum parkii (shea) butter, camellia sinensis (green tea) extract, cocos nucifera (coconut) oil, eucalyptus globulus (eucalyptus) oil, gluconolactone, glycerin, helianthus annuus (sunflower) seed oil, lecithin, simmondsia chinensis (jojoba) oil, tocopherol (vitamin e), xanthan gum

For maximum effectiveness:

Protect this product from excessive heat and direct sunlight.